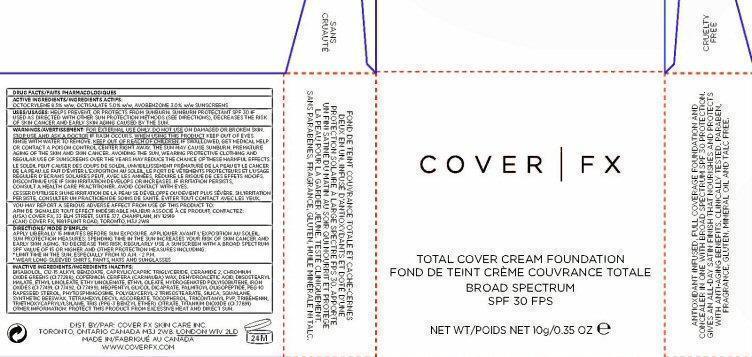 DRUG LABEL: COVER FX TOTAL COVER FOUNDATION
NDC: 68327-010 | Form: CREAM
Manufacturer: Cover FX Skin Care, Inc.
Category: otc | Type: HUMAN OTC DRUG LABEL
Date: 20131028

ACTIVE INGREDIENTS: OCTOCRYLENE 8.5 mg/1 g; OCTISALATE 5 mg/1 g; AVOBENZONE 3 mg/1 g
INACTIVE INGREDIENTS: LEVOMENOL; ALKYL (C12-15) BENZOATE; MEDIUM-CHAIN TRIGLYCERIDES; CERAMIDE 2; CHROMIC OXIDE; CARNAUBA WAX; DEHYDROACETIC ACID; DIISOSTEARYL MALATE; ETHYL LINOLEATE; ETHYL LINOLENATE; ETHYL OLEATE; HYDROGENATED POLYBUTENE (370 MW); FERRIC OXIDE RED; FERRIC OXIDE YELLOW; FERROSOFERRIC OXIDE; NEOPENTYL GLYCOL DICAPRATE; PALMITOYL OLIGOPEPTIDE; PEG-10 RAPESEED STEROL; PHYTOSPHINGOSINE; SILICON DIOXIDE; SQUALANE; TETRAHEXYLDECYL ASCORBATE; TOCOPHEROL; TRICONTANYL POVIDONE (4 TRICONTANYL BRANCHES/REPEAT); TRIBEHENIN; TRIETHOXYCAPRYLYLSILANE; TITANIUM DIOXIDE

ACTIVE INGREDIENTS

DRUG FACTS
ACTIVE INGREDIENTS:
OCTOCRYLENE 8.5% W/W, OCTISALATE 5.0% W/W, AVOBENZONE 3.0% W/W

Purpose/USES

SUNSCREEN

KEEP OUT OF REACH OF CHILDREN. IF SWALLOWED, GET MEDICAL HELP OR CONTACT A POISON CONTROL CENTER RIGHT AWAY.

USES

HELPS PREVENT, OR PROTECTS FROM SUNBURN. SUNBURN PROTECTANT SPF 30 IF USED AS DIRECTED WITH OTHER SUN PROTECTION METHODS (SEE DIRECTIONS). DECREASES THE RISK OF SKIN CANCER AND EARLY SKIN AGING CAUSED BY THE SUN.

WARNINGS

WARNINGS: FOR EXTERNAL USE ONLY. DO NOT USE ON DAMAGED OR BROKEN SKIN. STOP USE AND ASK A DOCTOR IF RASH OCCURS. WHEN USING THIS PRODUCT KEEP OUT OF EYES. RINSE WITH WATER TO REMOVE. THE SUN MAY CAUSE SUNBURN, PREMATURE AGING OF THE SKIN AND SKIN CANCER. AVOIDING THE SUN, WEARING PROTECTIVE CLOTHING AND REGULAR USE OF SUNSCREENS OVER THE YEARS MAY REDUCE THE CHANCE OF THESE HARMFUL EFFECTS.
DISCONTINUE USE IF SKIN IRRITATION DEVELOPS OR INCREASES. IF IRRITATION PERSISTS, CONSULT A HEALTH CARE PRACTITIONER. AVOID CONTACT WITH EYES.
YOU MAY REPORT A SERIOUS ADVERSE EFFECT FROM USE OF THIS PRODUCT TO (USA) COVER FX 33 ELM STREET SUITE 377, CHAMPLAIN, NY 12919 (CAN) COVER FX, 1681 FLINT ROAD, TORONTO, M3J 2W8

DIRECTIONS

APPLY LIBERALLY 15 MINUTES BEFORE SUN EXPOSURE.
SUN PROTECTION MEASURES; SPENDING TIME IN THE SUN INCREASES YOUR RISK OF SKIN CANCER AND EARLY SKIN AGING. TO DECREASE THIS RISK, REGULARLY USE A SUNSCREEN WITH A BROAD SPECTRUM SPF VALUE OF 15 OR HIGHER AND OTHER PROTECTION MEASURES INCLUDING:

- LIMIT TIME IN THE SUN, ESPECIALLY FROM 10 A.M. - 2 P.M.

- WEAR LONG SLEEVED SHIRTS, PANTS, HATS, AND SUNGLASSES

OTHER INFORMATION

ANTIOXIDANT INFUSED FULL COVERAGE FOUNDATION AND CONCEALER IN ONE WITH BROAD SPECTRUM SPF 30 PROTECTION. GIVES AN ALL-DAY SATIN FINISH THAT NOURISHES AND PROTECTS WITH ANTI-AGING BENEFITS. CLINICALLY TESTED. PARABEN, FRAGRANCE, GLUTEN, MINERAL OIL AND TALC FREE.

OTHER INFORMATION: PROTECT THIS PRODUCT FROM EXCESSIVE HEAT AND DIRECT SUN.

INACTIVE INGREDIENTS

BISABOLOL, C12-15 ALKYL BENZOATE, CAPRYLIC/CAPRIC TRIGLYCERIDE, CERAMIDE 2, CHROMIUM OXIDE BREENS (CL 77288), COPERNICIA CERIFERA (CARNAUBA) WAX, DEHYDROACETIC ACID, DIISOSTEARYL MALATE, ETHYL LINOLEATE, ETHYL LINOLENATE, ETHYL OLEATE, HYDROGENATEDD POLYISOBUTENE, IRON OXIDES (CL 77491, CL 77499, CL 77499), NEOPENTYL GLYCOL DICAPRATE, PALMITOYL OLIGOPEPTIDE, PEG-10 RAPESEED STEROL, PHYTOSPHINGOSINE, POLYGLYCERL-2 TRIISOSSTEARATE, SILICA, SQUALANE, SYNTHETIC BEESWAX, TETRAHEXYLDECYL ASCORBATE, TOCOPHEROL, TRICONTANYL PVP, TRIBEHENIN, TRIETHOXYCAPRYLYLSILANE, TRIS (PPG-3 BENTZYL ETHER) CITRATE, TITANIUM DIOXIDE (CL 77891)

PRODUCT LABEL

COVER l FX

TOTAL COVER CREAM FOUNDATION

BROAD SPECTRUM

SPF 30

NET WT/ 10G/0.35 OZ e

CRUELTY FREE

DIST. BY COVER FX SKIN CARE INC.

TORONTO, ONTARIO CANADA M3J 2W8. LONDON W1V 2LD

MADE IN CANADA WWW.COVERFX.COM